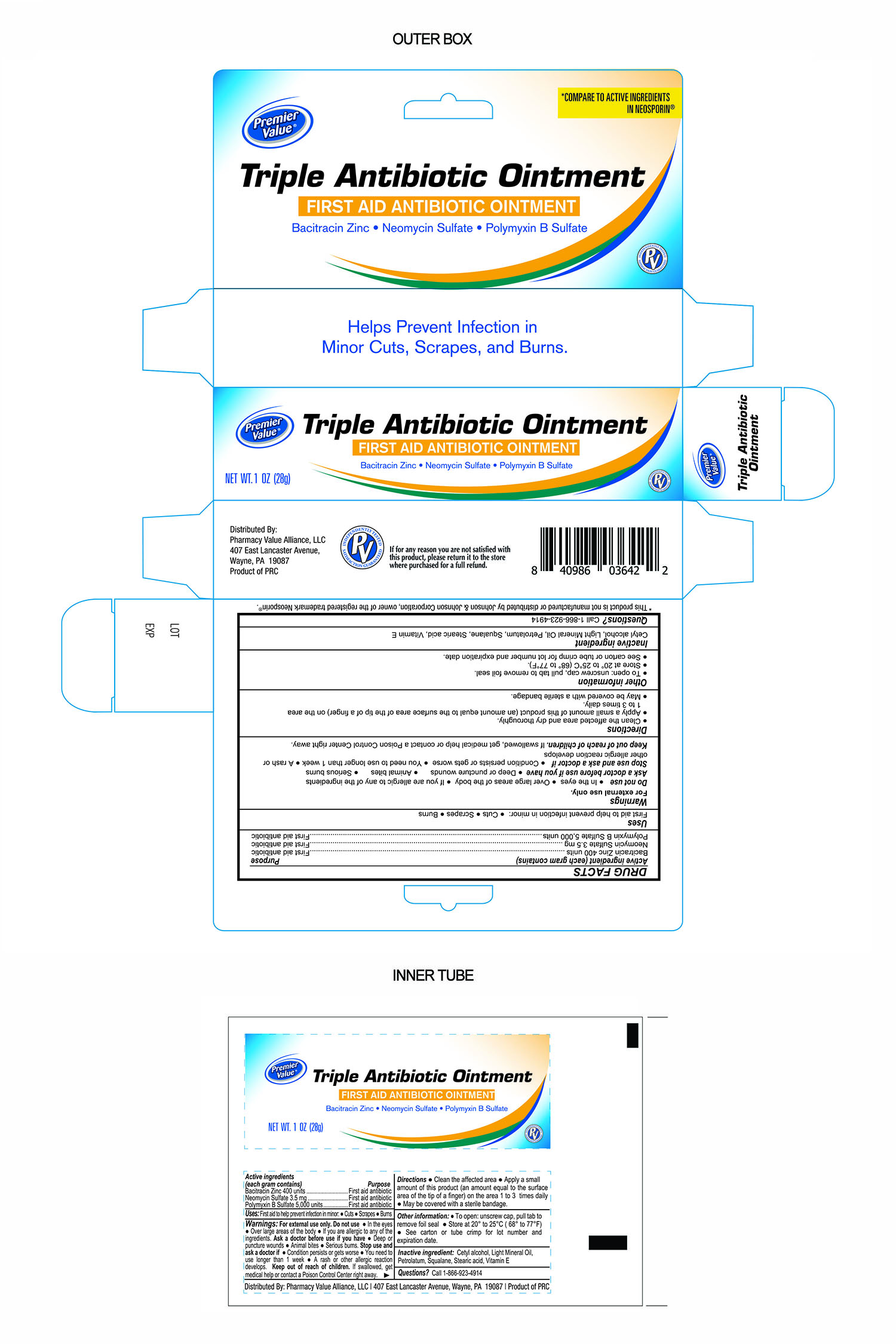 DRUG LABEL: Triple Antibiotic
NDC: 68016-319 | Form: OINTMENT
Manufacturer: Premier Value Alliance LLC.
Category: otc | Type: HUMAN OTC DRUG LABEL
Date: 20241220

ACTIVE INGREDIENTS: BACITRACIN ZINC 400 [USP'U]/1 g; NEOMYCIN SULFATE 3.5 mg/1 g; POLYMYXIN B SULFATE 5000 [USP'U]/1 g
INACTIVE INGREDIENTS: LIGHT MINERAL OIL; SQUALANE; PETROLATUM; CETYL ALCOHOL; STEARIC ACID; .ALPHA.-TOCOPHEROL

Premier Value Triple Antibiotic Ointment

Active ingredients (each gram contains)

Bacitracin zinc 400 units
Neomycin sulfate 3.5 mg
Polymyxin B sulfate 5,000 units

Purpose

First aid antibiotic

Keep out of reach of children. If swallowed, get medical help or contact a Poison Control Center right away.

INDICATIONS AND USAGE

Uses first aid to help prevent infection in minor:● cuts ● scrapes ● burns

Warnings For external use only.

Do not use ● in the eyes ● over large areas of the body

● if you are allergic to any of the ingredients.

Ask a doctor before use if you have

● deep or puncture wounds ● animal bites ● serious burns.

Stop use and ask a doctor if ● condition persists or gets worse

● you need to use longer than 1 week

● a rash or other allergic reaction develops

Inactive ingredient:Cetyl Alcohol, Light Mineral Oil, Squalane, Stearic Acid, Vitamin E and Petrolatum

Other information

● To open: unscrew cap, pull tab to remove foil seal
● store at 20° to 25°C (68° to 77°F)

● see carton or tube for lot number and expiration date.

Questions? Call 1-866-923-4914

Other Information

Distributed By:

Pharmacy Value Alliance, LLC.

407 East Lancaster Avenue, Wayne, PA. 19087

Product of PRC

If for any reason you are not satisfied with this product, please return it to the store where purchased for a full refund.

Directions

Clean the affected area and dry thoroughly.

Apply a small amount of this product (an amount equal to the surface area of the tip of a finger) on the area 1 to 3 times daily.

May be covered with a sterile bandage.